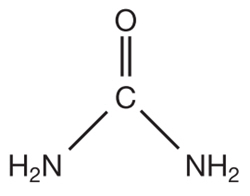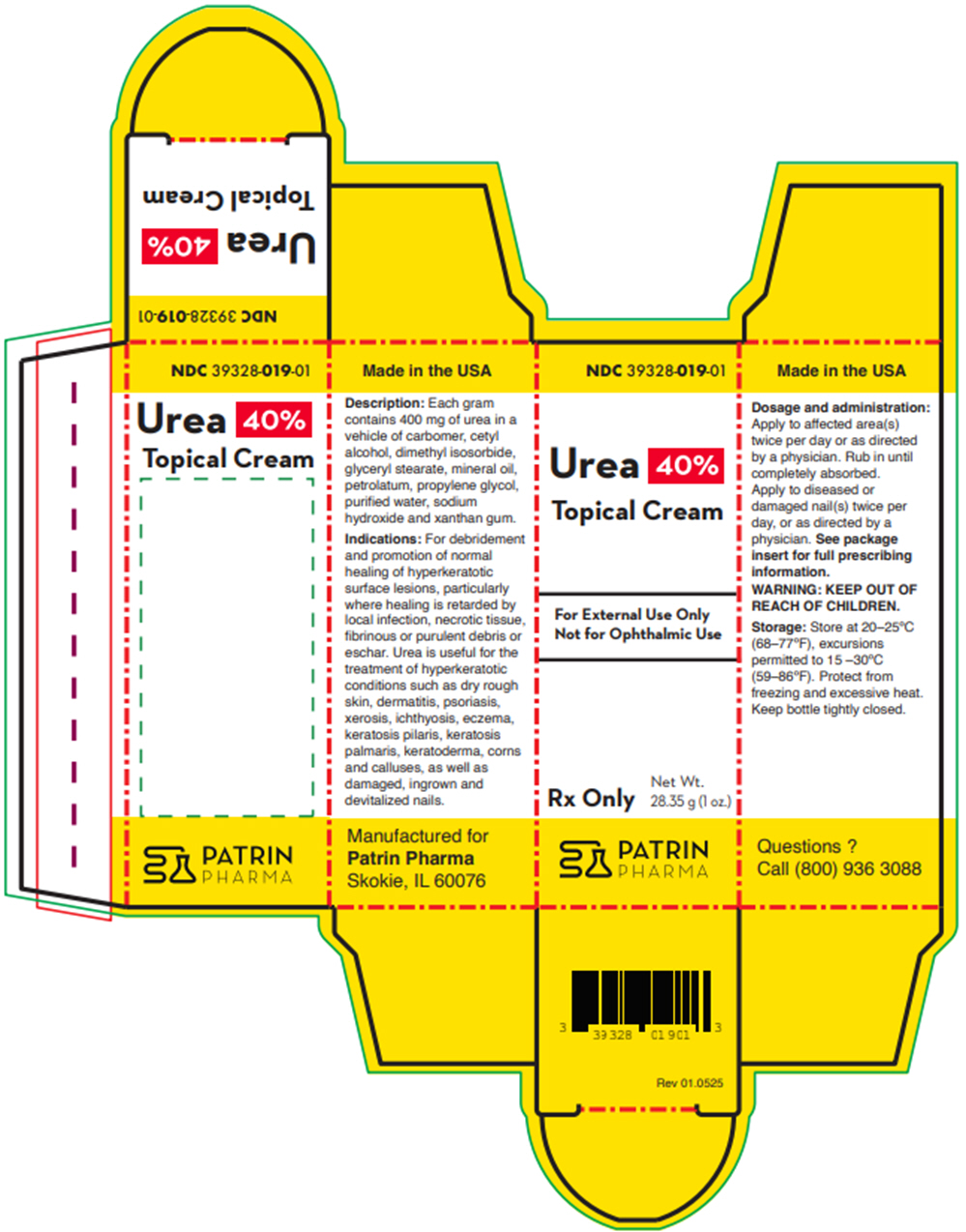 DRUG LABEL: Urea 40%
NDC: 39328-019 | Form: CREAM
Manufacturer: Patrin Pharma, Inc
Category: prescription | Type: HUMAN PRESCRIPTION DRUG LABEL
Date: 20250821

ACTIVE INGREDIENTS: Urea 400 mg/1 g
INACTIVE INGREDIENTS: CARBOMER HOMOPOLYMER, UNSPECIFIED TYPE; Cetyl alcohol; Dimethyl isosorbide; Glyceryl monostearate; Mineral oil; Petrolatum; Propylene glycol; Water; Sodium Hydroxide; Xanthan gum

Urea 40% Topical Cream

Rx Only

FOR EXTERNAL USE ONLY. NOT FOR OPHTHALMIC USE.

DESCRIPTION

Each gram contains 400 mg of urea in a vehicle of carbomer, cetyl alcohol, dimethyl isosorbide, glyceryl stearate, mineral oil, petrolatum, propylene glycol, purified water, sodium hydroxide, and xanthan gum.

Urea is a diamide of carbonic acid with the chemical structure:

CLINICAL PHARMACOLOGY

Urea gently dissolves the intercellular matrix which results in loosening the horny layer of skin and shedding scaly skin at regular intervals, thereby softening hyperkeratotic areas of the skin.

Pharmacokinetics

The mechanism of action of topically applied urea is not yet known.

INDICATIONS

For debridement and promotion of normal healing of hyperkeratotic surface lesions, particularly where healing is retarded by local infection, necrotic tissue, fibrinous or purulent debris or eschar. Urea is useful for the treatment of hyperkeratotic conditions such as dry rough skin, dermatitis, psoriasis, xerosis, ichthyosis, eczema, keratosis pilaris, keratosis palmaris, keratoderma, corns and calluses, as well as damaged, ingrown and devitalized nails.

CONTRAINDICATIONS

This product is contraindicated in people with known or suspected hypersensitivity to any of the ingredients of the product.

WARNING

KEEP OUT OF REACH OF CHILDREN.

PRECAUTIONS

FOR EXTERNAL USE ONLY. NOT FOR OPHTHALMIC USE.

General

This product is to be used as directed by a physician and should not be used to treat any condition other than that for which it was prescribed. If redness or irritation occurs, discontinue use and consult a physician.

Information for Patients

Patients should discontinue the use of this product if the condition becomes worse or if a rash develops in the area being treated or elsewhere. Avoid contact with eyes, lips and mucous membranes.

Carcinogenesis, Mutagenesis and Impairment of Fertility

Long-term animal studies for carcinogenic potential have not been performed on this product. Studies on reproduction and fertility also have not been performed.

Pregnancy

Category C

Animal reproduction studies have not been conducted with this product. It is also not known whether this product can affect reproduction capacity or cause fetal harm when administered to a pregnant woman. This product should be used by a pregnant woman only if clearly needed or when potential benefits outweigh potential hazards to the fetus.

Nursing Mothers

It is not known whether this drug is excreted in human milk. Because many drugs are excreted in human milk, caution should be exercised when this product is administered to a nursing woman.

ADVERSE REACTIONS

Transient stinging, burning, itching or irritation may occur and will normally disappear upon discontinuing the use of this product.

DOSAGE AND ADMINISTRATION

Apply to affected area(s) twice per day or as directed by a physician. Rub in until completely absorbed.

Apply to diseased or damaged nail(s) twice per day, or as directed by a physician.

STORAGE

Store at 20–25°C (68–77ºF), excursions permitted to 15–30ºC (59–86ºF). Protect from freezing and excessive heat. Keep bottle tightly closed

HOW SUPPLIED

28.35 g (1 oz.) bottles, NDC 39328-019-01

85 g (3 oz.) bottles, NDC 39328-019-03

198.4 g (7 oz.) bottles, NDC 39328-019-07

To report SUSPECTED ADVERSE REACTIONS, contact Patrin Pharma at 1-800-936-3088 or FDA at 1-800-FDA-1088 or www. fda.gov/medwatch for voluntary reporting of suspected adverse reactions.

Made in the USA
Manufactured for:
Patrin Pharma
Skokie, IL 60076
Questions (800) 936 3088

Rev 01.0525

PRINCIPAL DISPLAY PANEL - 28.35 g Bottle Carton

NDC 39328-019-01

Urea 40%
Topical Cream

For External Use Only
Not for Ophthalmic Use

Rx Only

Net Wt.
28.35 g (1 oz.)

PATRIN
PHARMA